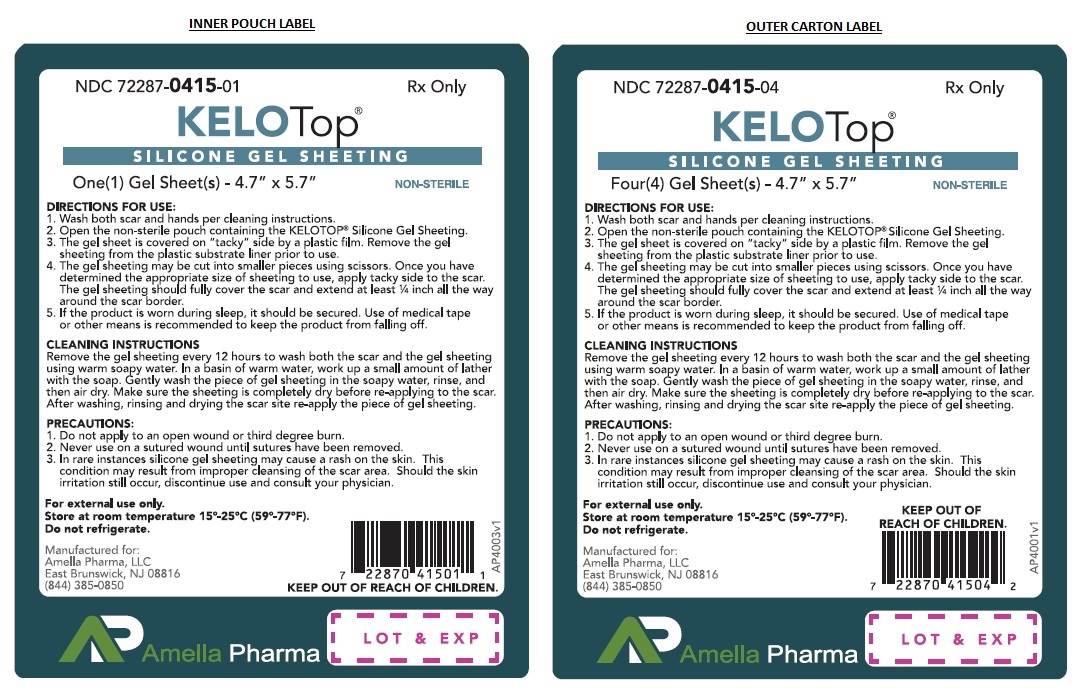 DRUG LABEL: Kelotop
NDC: 72287-415
Manufacturer: AMELLA PHARMA, LLC
Category: other | Type: MEDICAL DEVICE
Date: 20181226

KELOTop®

KELOTOP® - DIMETHYL METHYLHYDROGEN METHYLVINYL SILICONE GEL, ORGANOPOLYSILOXANE, SILICONE GEL SHEETING

Rx Only

For external use only

Not for ophthalmic use

INDICATIONS

KELOTOP® is intended for use in the management, control and prevention of old and new hypertrophic or keloid scars resulting from burns or surgical or traumatic injury of the skin, by forming an occlusive barrier.

CONTRAINDICATIONS

Do not use on open wounds or when any Dermatological conditions disrupt the skin (such as a rash).

KELOTOP® is contraindicated in patients with known hypersensitivity to silicone or any of the listed ingredients.

WARNINGS, PRECAUTIONS, ADVERSE REACTIONS

Possible complications include:
• Superficial maceration of the skin
• Rash
• Skin Discoloration
• Pruritus
• Sheeting tack and thickness vary

Rashes have been observed on skin under the KELOTOP®, this has been attributed to poor or insufficient hygiene. Similar rashes have been attributed to KELOTOP® being wrapped too tightly. Should a rash occur, stop using the KELOTOP® for 12 hours followed by using the KELOTOP® for 12 hours. If the rash persists, a physician should be contacted and gel sheeting use should be discontinued.

Discoloration of the skin covered by KELOTOP® has been reported, particularly in dark skinned patients. This effect appears to be transient, and may be similar to the discoloration experienced whenever an area of skin is covered for extended periods of time. If ingested, get medical help or contact Poison Control Center right away.

Some patients report differences in KELOTOP® surface tack and thickness from sheet to sheet. Perception of tack is subjective and the adhesive characteristic of KELOTOP® may vary. These variations do not affect the function of the product.

Small bubbles may form on the KELOTOP® after repeated washing and use. This does not have an impact on the function of the product. This medication should be used as directed by your physician during pregnancy or while breastfeeding. Consult your doctor about the risks and benefits.

Do not use creams, lotions, sun block or other silicone products on your skin when wearing KELOTOP®. These products will create a barrier between the scar site and the silicone gel, preventing a proper healing environment.

Call your doctor about side effects. You may report side effects to FDA at 1-800-FDA-1088. KEEP OUT OF REACH OF CHILDREN.

PRECAUTIONS:

1. Do not apply to an open wound or third degree burn.
2. Never use on a sutured wound until sutures have been removed.
3. In rare instances silicone gel sheeting may cause a rash on the skin. This condition may result from improper cleansing of the scar area. Should the skin irritation still occur, discontinue use and consult your physician

INGREDIENTS

Each KELOTOP® Silicone Gel Sheet contains: Dimethyl methylhydrogen methylvinyl silicone gel, Organopolysiloxane.

INSTRUCTIONS FOR USE:

1. Wash both scar and hands per cleaning instructions.
2. Open the non-sterile pouch containing the KELOTOP®.
3. The gel sheet is covered on "tacky" side by a plastic film. Remove the KELOTOP® from the plastic substrate liner prior to use.
4. The gel sheet may be cut into smaller pieces using scissors. Once you have determined the appropriate size of sheeting to use, apply tacky side to the scar. The gel sheeting should fully cover the scar and extend atleast ¼ inch all the way around the scar border.
5. If the product is worn during sleep, it should be secured. Use of medical tape or other means is recommended to keep the product from falling off.

CLEANING INSTRUCTIONS Remove the gel sheeting every 12 hours to wash both the scar and the KELOTOP®. In a basin of warm water, work up a small amount of lather with the soap. Gently wash the piece of gel sheeting in the soapy water, rinse, and then air dry. Make sure the sheeting is completely dry before re-applying to the scar. After washing, rinsing and drying the scar site re-apply the piece of gel sheeting.

WEARING TIME Optimal wearing time for KELOTOP® is 24 hours per day. If it is not possible to wear the gel sheet for the recommended 24 hour period, a minimum of 12 hours per day is required, washing per the instructions above once in that period. Follow this procedure each day, washing and re-applying the gel sheeting to the scar for 7 days. At that time the piece of gel sheeting will begin to lose its adhesive quality and/or may become embedded with surface dirt. It is recommended to discard the piece of gel sheeting and apply a new piece.

The overall optimal period of use is usually 8 to 12 weeks.

HOW IT IS SUPPLIED

KELOTOP® are supplied as a clear gel matrix sheet sized 4.7” x 5.7” with a pink mylar cover to protect the sticky side, and a thick white translucent reusable mylar cover to protect the KELOTOP® between uses. Non-sterile product is labeled as such and supplied in a protective package within a protective outer container.

KELOTOP® is available as the following:
NDC 72287-415-04 4ct envelope

Store at 15°-25°C (59° to 77°F); Keep away from heat and protect from freezing. Do not refrigerate.

NON-STERILE

Manufactured for:
Amella Pharma, LLC
East Brunswick, NJ 08816

12/2018 AP-4002v2
KELOTOP® is a registered Trademark of Amella Pharma, LLC